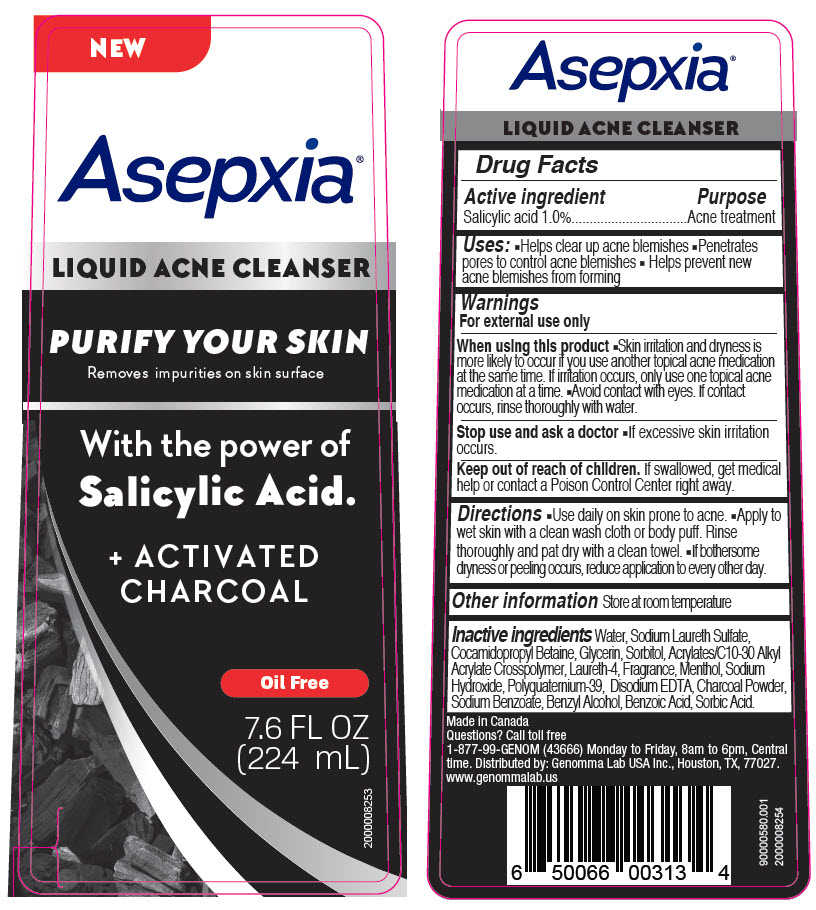 DRUG LABEL: Asepxia Liquid Acne Cleanser
NDC: 50066-060 | Form: LOTION
Manufacturer: Genomma Lab USA
Category: otc | Type: HUMAN OTC DRUG LABEL
Date: 20190926

ACTIVE INGREDIENTS: Salicylic Acid 10 mg/1 mL
INACTIVE INGREDIENTS: Sodium Laureth-3 Sulfate; Glycerin; Sorbitol; Cocamidopropyl betaine; Laureth-4; Activated Charcoal

Asepxia® Liquid Acne Cleanser

Drug Facts

Active ingredient

Salicylic acid 1.0%

Purpose

Acne treatment

Uses

- Helps clear up acne blemishes
- Penetrates pores to control acne blemishes
- Helps prevent new acne blemishes from forming

Warnings

For external use only

When using this product

- Skin irritation and dryness is more likely to occur if you use another topical acne medication at the same time. If irritation occurs, only use one topical acne medication at a time.
- Avoid contact with eyes. If contact occurs, rinse thoroughly with water.

Stop use and ask a doctor

- If excessive skin irritation occurs.

Keep out of reach of children. If swallowed, get medical help or contact a Poison Control Center right away.

Directions

- Use daily on skin prone to acne.
- Apply to wet skin with a clean wash cloth or body puff. Rinse thoroughly and pat dry with a clean towel.
- If bothersome dryness or peeling occurs, reduce application to every other day.

Other information

Store at room temperature

Inactive ingredients

Water, Sodium Laureth Sulfate, Cocamidopropyl Betaine, Glycerin, Sorbitol, Acrylates/C10-30 Alkyl Acrylate Crosspolymer, Laureth-4, Fragrance, Menthol, Sodium Hydroxide, Polyquaternium-39, Disodium EDTA, Charcoal Powder, Sodium Benzoate, Benzyl Alcohol, Benzoic Acid, Sorbic Acid.

Questions?

Call toll free 1-877-99-GENOM (43666) Monday to Friday, 8am to 6pm, Central time.

Distributed by: Genomma Lab USA Inc., Houston, TX, 77027.

PRINCIPAL DISPLAY PANEL - 224 mL Bottle Label

NEW

Asepxia®

LIQUID ACNE CLEANSER

PURIFY YOUR SKIN
Removes impurities on skin surface

With the power of
Salicylic Acid.

+ ACTIVATED
CHARCOAL

Oil Free

7.6 FL OZ
(224 mL)

2000008253